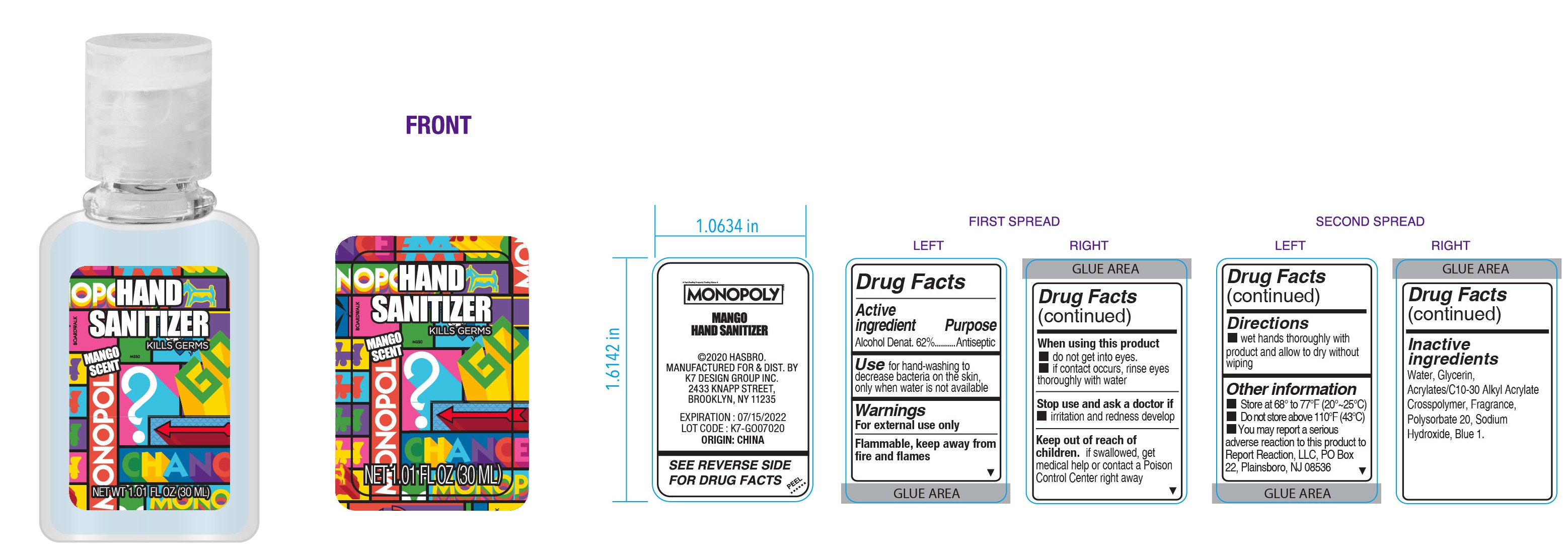 DRUG LABEL: MONOPOLY Hand Sanitizer
NDC: 51522-041 | Form: GEL
Manufacturer: Gold Orient International Limited
Category: otc | Type: HUMAN OTC DRUG LABEL
Date: 20200724

ACTIVE INGREDIENTS: ALCOHOL 62 mL/100 mL
INACTIVE INGREDIENTS: WATER; SODIUM HYDROXIDE; FD&C BLUE NO. 1; POLYSORBATE 20; GLYCERIN; CARBOMER COPOLYMER TYPE A (ALLYL PENTAERYTHRITOL CROSSLINKED)

MONOPOLY Hand Sanitizer 100

Active ingredient

Alcohol Denat. 62%

Purpose

Antiseptic

Use

for hand-washing to decrease bacteria on the skin, only when water is not available

Warnings

For external use only

When using this product

- do not get into eyes
- if contact occurs, rinse eyes thorouly with water

Stop use and ask a doctor if

- irritation and redness develop

Keep out of reach of children.

if swallowed, get medical help or contact a Poison Control Center right away

Directions

- wet hands thorouly with product and allow to dry without wiping

Other information

- Store at 68° to 77°F (20°~25°C)
- Do not store above 110°F(43°C)
- You may report a serious adverse reaction to this product to Report Reaction, LLC, PO Box 22, Plainsboro, NJ 08536

Inactive ingredients

Water, Glycerin, Acrylates/C10-30 Alkyl Acrylate Crosspolymer, Fragrance, Polysorbate 20, Sodium Hydroxide, Blue 1.